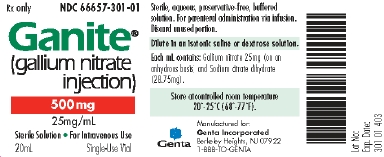 DRUG LABEL: GANITE
NDC: 66657-301 | Form: INJECTION, SOLUTION, CONCENTRATE
Manufacturer: Genta Incorporated
Category: prescription | Type: HUMAN PRESCRIPTION DRUG LABEL
Date: 20120319

ACTIVE INGREDIENTS: GALLIUM NITRATE 25 mg/1 mL
INACTIVE INGREDIENTS: TRISODIUM CITRATE DIHYDRATE

Ganite® (gallium nitrate injection)

WARNING

Concurrent use of gallium nitrate with other potentially nephrotoxic drugs (e.g., aminoglycosides, amphotericin B) may increase the risk for developing severe renal insufficiency in patients with cancer-related hypercalcemia. If use of a potentially nephrotoxic drug is indicated during gallium nitrate therapy, gallium nitrate administration should be discontinued and it is recommended that hydration be continued for several days after administration of the potentially nephrotoxic drug. Serum creatinine and urine output should be closely monitored during and subsequent to this period. Ganite therapy should be discontinued if the serum creatinine level exceeds 2.5 mg/dL.

DESCRIPTION

Gallium nitrate injection is a clear, colorless, odorless, sterile solution of gallium nitrate, a hydrated nitrate salt of the group IIIa element, gallium. Gallium nitrate is formed by the reaction of elemental gallium with nitric acid, followed by crystallization of the drug from the solution. The stable, nonahydrate, Ga(N03)3•9H2O is a white, slightly hygroscopic, crystalline powder of molecular weight 417.87, that is readily soluble in water. Each mL of Ganite (gallium nitrate injection) contains gallium nitrate 25 mg (on an anhydrous basis) and sodium citrate dihydrate 28.75 mg. The solution may contain sodium hydroxide or hydrochloric acid for pH adjustment to 6.0-7.0.

CLINICAL PHARMACOLOGY

Mechanism of Action Ganite exerts a hypocalcemic effect by inhibiting calcium resorption from bone, possibly by reducing increased bone turnover. Although in vitro and animal studies have been performed to investigate the mechanism of action of gallium nitrate, the precise mechanism for inhibiting calcium resorption has not been determined. No cytotoxic effects were observed on bone cells in drug-treated animals.

Pharmacokinetics Gallium nitrate was infused at a daily dose of 200 mg/m^2 for 5 (n=2) or 7 (n=10) consecutive days to 12 cancer patients. In most patients apparent steady-state is achieved by 24 to 48 hours. The range of average steady-state plasma levels of gallium observed among 7 fully evaluable patients was between 1134 and 2399 ng/mL. The average plasma clearance of gallium (n=7) following daily infusion of gallium nitrate at a dose of 200 mg/m^2 for 5 or 7 days was 0.15 L/hr/kg (range: 0.12 to 0.20 L/hr/kg). In one patient who received daily infusion doses of 100, 150 and 200 mg/m^2 the apparent steady-state levels of gallium did not increase proportionally with an increase in dose. Gallium nitrate is not metabolized either by the liver or the kidney and appears to be significantly excreted via the kidney. Urinary excretion data for a dose of 200 mg/m^2 has not been determined.

Cancer-Related Hypercalcemia Hypercalcemia is a common problem in hospitalized patients with malignancy. It may affect 10-20% of patients with cancer. Different types of malignancy seem to vary in their propensity to cause hypercalcemia. A higher incidence of hypercalcemia has been observed in patients with non-small cell lung cancer, breast cancer, multiple myeloma, kidney cancer, and cancer of head and neck. Hypercalcemia of malignancy seems to result from an imbalance between the net resorption of bone and urinary excretion of calcium. Patients with extensive osteolytic bone metastases frequently develop hypercalcemia: this type of hypercalcemia is common with primary breast cancer. Some of these patients have been reported to have increased renal tubular calcium resorption. Breast cancer cells have been reported to produce several potential bone-resorbing factors which stimulate the local osteoclast activity. Humoral hypercalcemia is common with the solid tumors of the lung, head and neck, kidney, and ovaries. Systemic factors (e.g., PTH-rP) produced either by the tumor or host cells have been implicated for the altered calcium fluxes between the extracellular fluid, the kidney, and the skeleton. About 30% of patients with myeloma develop hypercalcemia associated with extensive osteolytic lesions and impaired glomerular filtration. Myeloma cells have been reported to produce local factors that stimulate adjacent osteoclasts.

Hypercalcemia may produce a spectrum of signs and symptoms including: anorexia, lethargy, fatigue, nausea, vomiting, constipation, dehydration, renal insufficiency, impaired mental status, coma and cardiac arrest. A rapid rise in serum calcium may cause more severe symptoms for a given level of hypercalcemia. Since calcium is bound to serum proteins, which may fluctuate in concentration as a response to changes in blood volume, changes in total serum calcium (especially during rehydration) may not accurately reflect changes in the concentration of free-ionized calcium. In the absence of a direct measurement of free-ionized calcium, measurement of the serum albumin concentration and correction of the total serum calcium concentration may help in assessing the severity of hypercalcemia. The patient’s acid-base status should also be taken into consideration while assessing the degree of hypercalcemia. Mild or asymptomatic hypercalcemia may be treated with conservative measures (i.e., saline hydration, with or without diuretics). The patient’s cardiovascular status should be taken into consideration in the use of saline. In patients who have an underlying cancer type that may be sensitive to corticosteroids (e.g., hematologic cancers), the use or addition of corticosteroid therapy may be indicated.

Hypocalcemic Activity A randomized double-blind clinical study comparing Ganite with calcitonin was conducted in patients with a serum calcium concentration (corrected for albumin) ≥ 12.0 mg/dL following 2 days of hydration. Ganite was given as a continuous intravenous infusion at a dose of 200 mg/m^2/day for 5 days and calcitonin was given intramuscularly at a dose of 8 I.U./kg every 6 hours for 5 days. Elevated serum calcium (corrected for albumin) was normalized in 75% (18 of 24) of the patients receiving Ganite and in 27% (7 of 26) of the patients receiving calcitonin (p=0.0016). The time-course of effect on serum calcium (corrected for albumin) is summarized in the following table.

Change in Corrected Serum Calcium by Time from Initiation of Treatment
Time Period^1 (hours) | Mean Change in Serum Calcium^2 (mg/dL)
 | GANITE | Calcitonin
24 | -0.4 | -1.6*
48 | -0.9 | -1.4
72 | -1.5 | -1.1
96 | -2.9* | -1.1
120 | -3.3* | -1.3
^1 Time after initiation of therapy in hours.
^2 Change from baseline in serum calcium (corrected for albumin).
* Comparison between treatment groups (p< 0.01).

The median duration of normocalcemia/hypocalcemia was 7.5 days for patients treated with Ganite and 1 day for patients treated with calcitonin. A total of 92% of patients treated with Ganite had a decrease in serum calcium (corrected for albumin) ≥ 2.0 mg/dL as compared to 54% of the patients treated with calcitonin (p=0.004).

An open-label, non-randomized study was conducted to examine a range of doses and dosing schedules of Ganite for control of cancer-related hypercalcemia. The principal dosing regimens were 100 and 200 mg/m^2/day, administered as continuous intravenous infusions for 5 days. Ganite, at a dose of 200 mg/m^2/day for 5 days was found to normalize elevated serum calcium levels (corrected for albumin) in 83% of patients as compared to 50% of patients receiving a dose of 100 mg/m^2/day for 5 days. A decrease in serum calcium (corrected for albumin) ≥ 2.0 mg/dL was observed in 83% and 94% of patients treated with Ganite at dosages of 100 and 200 mg/m^2/day for 5 days, respectively. There were no significant differences in the proportion of patients responding to Ganite when considering either the presence or absence of bone metastasis, or whether the tumor histology was epidermoid or nonepidermoid.

INDICATIONS AND USAGE

Ganite is indicated for the treatment of clearly symptomatic cancer-related hypercalcemia that has not responded to adequate hydration. In general, patients with a serum calcium (corrected for albumin) < 12 mg/dL would not be expected to be symptomatic. Mild or asymptomatic hypercalcemia may be treated with conservative measures (i.e., saline hydration, with or without diuretics). In the treatment of cancer-related hypercalcemia, it is important first to establish adequate hydration, preferably with intravenous saline, in order to increase the renal excretion of calcium and correct dehydration caused by hypercalcemia.

CONTRAINDICATIONS

Ganite should not be administered to patients with severe renal impairment (serum creatinine > 2.5 mg/dL).

WARNINGS

(See boxed WARNING.) The hypercalcemic state in cancer patients is commonly associated with impaired renal function. Abnormalities in renal function (elevated BUN and/or serum creatinine) have been observed in clinical trials with Ganite. It is strongly recommended that serum creatinine be monitored during Ganite therapy. Since patients with cancer-related hypercalcemia are frequently dehydrated, it is important that such patients be adequately hydrated with oral and/or intravenous fluids (preferably saline) and that a satisfactory urine output (a urine output of 2 L/day is recommended) be established before therapy with Ganite is started. Adequate hydration should be maintained throughout the treatment period, with careful attention to avoid overhydration in patients with compromised cardiovascular status. Diuretic therapy should not be employed prior to correction of hypovolemia. Ganite therapy should be discontinued if the serum creatinine level exceeds 2.5 mg/dL.

The use of Ganite in patients with marked renal insufficiency (serum creatinine > 2.5 mg/dL) has not been systematically examined. If therapy is undertaken in patients with moderately impaired renal function (serum creatinine 2.0 to 2.5 mg/dL), frequent monitoring of the patient’s renal status is recommended. Treatment should be discontinued if the serum creatinine level exceeds 2.5 mg/dL.

Combined use of Ganite with other potentially nephrotoxic drugs (e.g., aminoglycosides, amphotericin B) may increase the risk of developing renal insufficiency in patients with cancer-related hypercalcemia (see boxed WARNING).

PRECAUTIONS

General Asymptomatic or mild to moderate hypocalcemia (6.5 - 8.0 mg/dL, corrected for serum albumin) occurred in approximately 38% of patients treated with Ganite in the controlled clinical trial. One patient exhibited a positive Chvostek’s sign. If hypocalcemia occurs, Ganite therapy should be stopped and short-term calcium therapy may be necessary.

Laboratory Tests Renal function (serum creatinine and BUN) and serum calcium must be closely monitored during Ganite therapy. In addition to baseline assessment, the suggested frequency of calcium and phosphorus determinations is daily and twice weekly, respectively. Ganite should be discontinued if the serum creatinine exceeds 2.5 mg/dL.

Drug Interactions The concomitant use of highly nephrotoxic drugs in combination with Ganite may increase the risk for development of renal insufficiency (see WARNINGS). Available information does not indicate any adverse interaction with diuretics such as furosemide. A symptom complex of dyspnea (associated with interstitial pneumonitis in some instances), mouth soreness, and asthenia has been reported in a small number of multiple myeloma patients receiving low dose (40 mg) gallium nitrate subcutaneously in addition to oral cyclophosphamide and prednisone. The serious nature of the underlying condition of these patients precludes a precise understanding of the relationship of these events to either gallium nitrate treatment alone or with cyclophosphamide.

Carcinogenesis, Mutagenesis, Impairment of Fertility Long-term studies in animals have not been performed to evaluate the carcinogenic potential of gallium nitrate. Gallium nitrate is not mutagenic in standard tests (i.e., Ames test and chromosomal aberration studies on human lymphocytes).

Usage in Pregnancy Pregnancy Category C. Animal reproduction studies have not been conducted with gallium nitrate. It is also not known whether gallium nitrate can cause fetal harm when administered to a pregnant woman or can affect reproductive capacity. Ganite should be administered to a pregnant woman only if clearly needed.

Nursing Mothers It is not known whether gallium nitrate is excreted in human milk. Because of the potential for serious adverse reactions in nursing infants from gallium nitrate, a decision should be made whether to discontinue nursing or discontinue the drug, taking into account the importance of the drug to the mother.

Pediatric Use The safety and effectiveness of Ganite in children have not been established.

ADVERSE REACTIONS

Kidney Adverse renal effects, as demonstrated by rising BUN and creatinine, have been reported in about 12.5% of patients treated with Ganite. In a controlled clinical trial of patients with cancer-related hypercalcemia, two patients receiving Ganite and one patient receiving calcitonin developed acute renal failure. Due to the serious nature of the patients’ underlying conditions, the relationship of these events to the drug was unclear. Ganite should not be administered to patients with serum creatinine >2.5 mg/dL (see CONTRAINDICATIONS and WARNINGS).

Metabolic Hypocalcemia may occur after Ganite treatment (see PRECAUTIONS).

Transient hypophosphatemia of mild-to-moderate degree may occur in up to 79% of hypercalcemic patients following treatment with Ganite. In a controlled clinical trial, 33% of patients had at least 1 serum phosphorus measurement between 1.5-2.4 mg/dL, while 46% of patients had at least 1 serum phosphorus value <1.5 mg/dL. Patients who develop hypophosphatemia may require oral phosphorus therapy.

Decreased serum bicarbonate, possibly secondary to mild respiratory alkalosis was reported in 40-50% of cancer patients treated with Ganite. The cause for this effect is not clear. This effect has been asymptomatic and has not required specific treatment.

Hematologic The use of very high doses of gallium nitrate (up to 1400 mg/m^2) in treating patients for advanced cancer has been associated with anemia, and several patients have received red blood cell transfusions. Due to the serious nature of the underlying illness, it is uncertain that the anemia was caused by gallium nitrate.

Blood Pressure A decrease in mean systolic and diastolic blood pressure was observed several days after treatment with gallium nitrate in a controlled clinical trial. The decrease in blood pressure was asymptomatic and did not require specific treatment.

Visual and Auditory In cancer chemotherapy trials, a small proportion (<1%) of patients treated with multiple high doses of gallium nitrate combined with other investigational anticancer drugs, have developed acute optic neuritis. While these patients were critically ill and had received multiple drugs, a reaction to high-dose gallium nitrate is possible. Most patients had full recovery; however, at least one case of permanent blindness has been reported. One patient with cancer-related hypercalcemia was reported to develop decreased hearing following gallium nitrate administration. Due to the patient’s underlying condition and concurrent therapies, the relationship of this event to gallium nitrate administration is unclear. Tinnitus and partial loss of auditory acuity have been reported rarely (<1%) in patients who received high-dose gallium nitrate as anticancer treatment.

Miscellaneous Other clinical events reported in association with gallium nitrate treatment for cancer as well as cancer-related hypercalcemia include: nausea and/or vomiting, tachycardia, lethargy, confusion, dreams and hallucinations, diarrhea, constipation, lower extremity edema, hypothermia, fever, dyspnea, rales and rhonchi, anemia, leukopenia, paresthesia, skin rash, pleural effusion, and pulmonary infiltrates. Due to the serious nature of the underlying condition of these patients, the relationship of these events to therapy with gallium nitrate is unknown. A single case of encephalopathy followed rapidly by coma and death has been reported after treatment in a cancer chemotherapy trial with gallium nitrate 300 mg/m^2/day for 7 days. Treatment with gallium nitrate other than as described in this labeling may be complicated by adverse events not listed.

OVERDOSAGE

Rapid intravenous infusion of gallium nitrate or use of doses higher than recommended (200 mg/m^2) may cause nausea and vomiting and a substantially increased risk of renal insufficiency. In the event of overdosage, further drug administration should be discontinued, serum calcium should be monitored, and the patient should receive vigorous intravenous hydration, with or without diuretics, for 2-3 days. During this time period, renal function and urinary output should be carefully monitored so that fluid intake and output are balanced.

DOSAGE AND ADMINISTRATION

The usual recommended dose of Ganite is 200 mg per square meter of body surface area (200 mg/m^2) daily for 5 consecutive days. In patients with mild hypercalcemia and few symptoms, a lower dosage of 100 mg/m^2/day for 5 days may be considered. If serum calcium levels are lowered into the normal range in less than 5 days, treatment may be discontinued early. The daily dose must be administered as an intravenous infusion over 24 hours. The daily dose should be diluted, preferably in 1,000 mL of 0.9% Sodium Chloride Injection USP, or 5% Dextrose Injection USP, for administration as an intravenous infusion over 24 hours. Adequate hydration must be maintained throughout the treatment period, with careful attention to avoid overhydration in patients with compromised cardiovascular status. Controlled studies have not been undertaken to evaluate the safety and effectiveness of retreatment with gallium nitrate.

When Ganite is added to either 0.9% Sodium Chloride Injection USP or 5% Dextrose Injection USP, it is stable for 48 hours at room temperature (15°C to 30°C) or for 7 days if stored under refrigeration (2°C to 8°C). Parenteral drug products should be inspected visually for particulate matter and discoloration prior to administration whenever solution and container permit.

HOW SUPPLIED

Ganite® (gallium nitrate injection) is supplied as a 5-unit carton, NDC 66657-301-05.

Each carton contains 5 single-dose, flip-top vials (NDC 66657-301-01) each containing 500 mg of gallium nitrate (25 mg/mL) in 20 mL.

Store at controlled room temperature 20°-25°C (68°-77°F).

Contains no preservative. Discard unused portion.

Rx only

Ganite® is a trademark of Genta Incorporated.

Manufactured for:
Genta Incorporated
Berkeley Heights, NJ 07922
1-888-TO-GENTA

Revised: October 2006

30105902

Principal Display Panel - Vial Label

Vial Label

Rx only NDC 66657-301-01

Ganite®

(gallium nitrate injection)

500mg

25mg/mL

Sterile Solution • For Intravenous Use

20mL Single-Use Vial

Sterile, aqueous, preservative-free, buffered
solution. For parenteral administration via infusion.
Discard unused portion.

Dilute in an isotonic saline or dextrose solution.

Each mL contains: Gallium nitrate 25mg (on an
anhydrous basis) and Sodium citrate dihydrate
(28.75mg).

Store at controlled room temperature
20°-25°C (68°-77°F).

Manufactured for:
Genta Incorporated
Berkeley Heights, NJ 07922
1-888-TO-GENTA